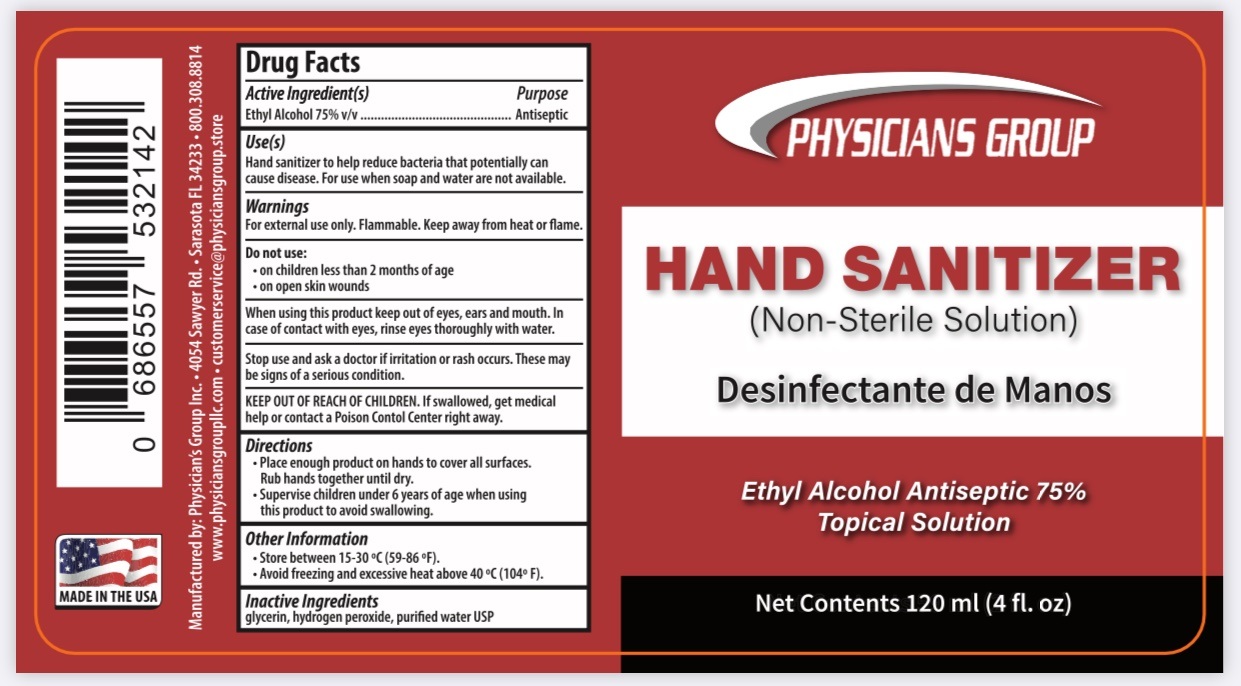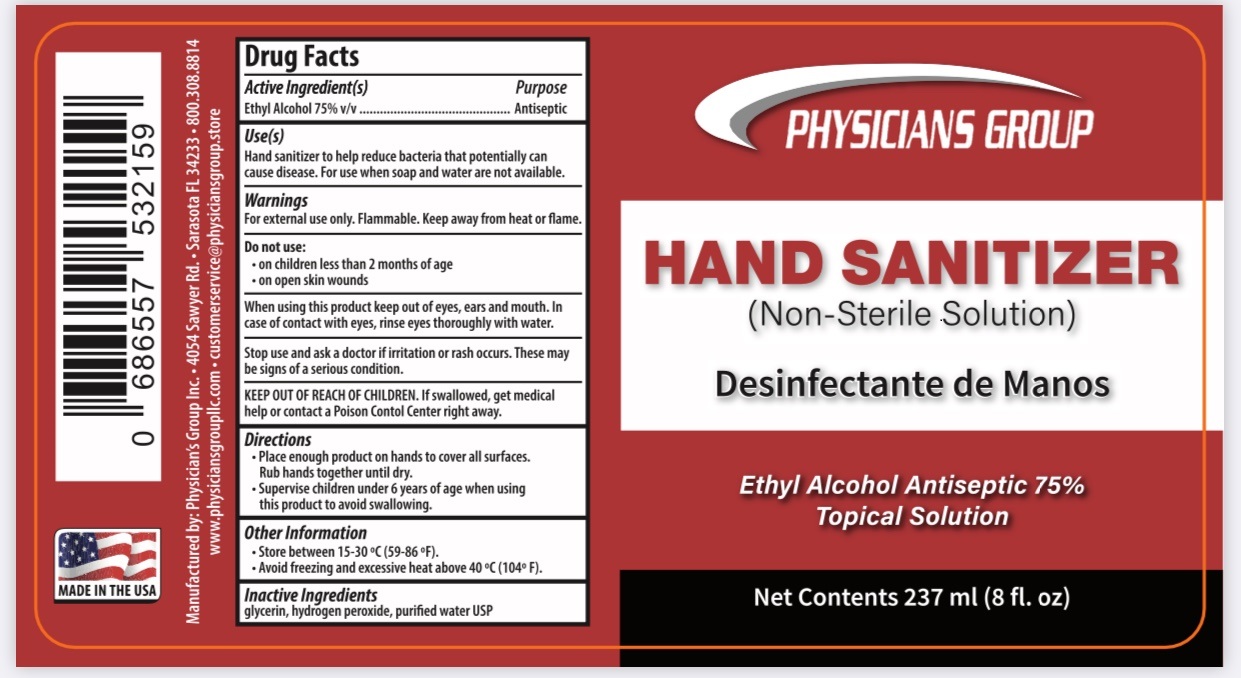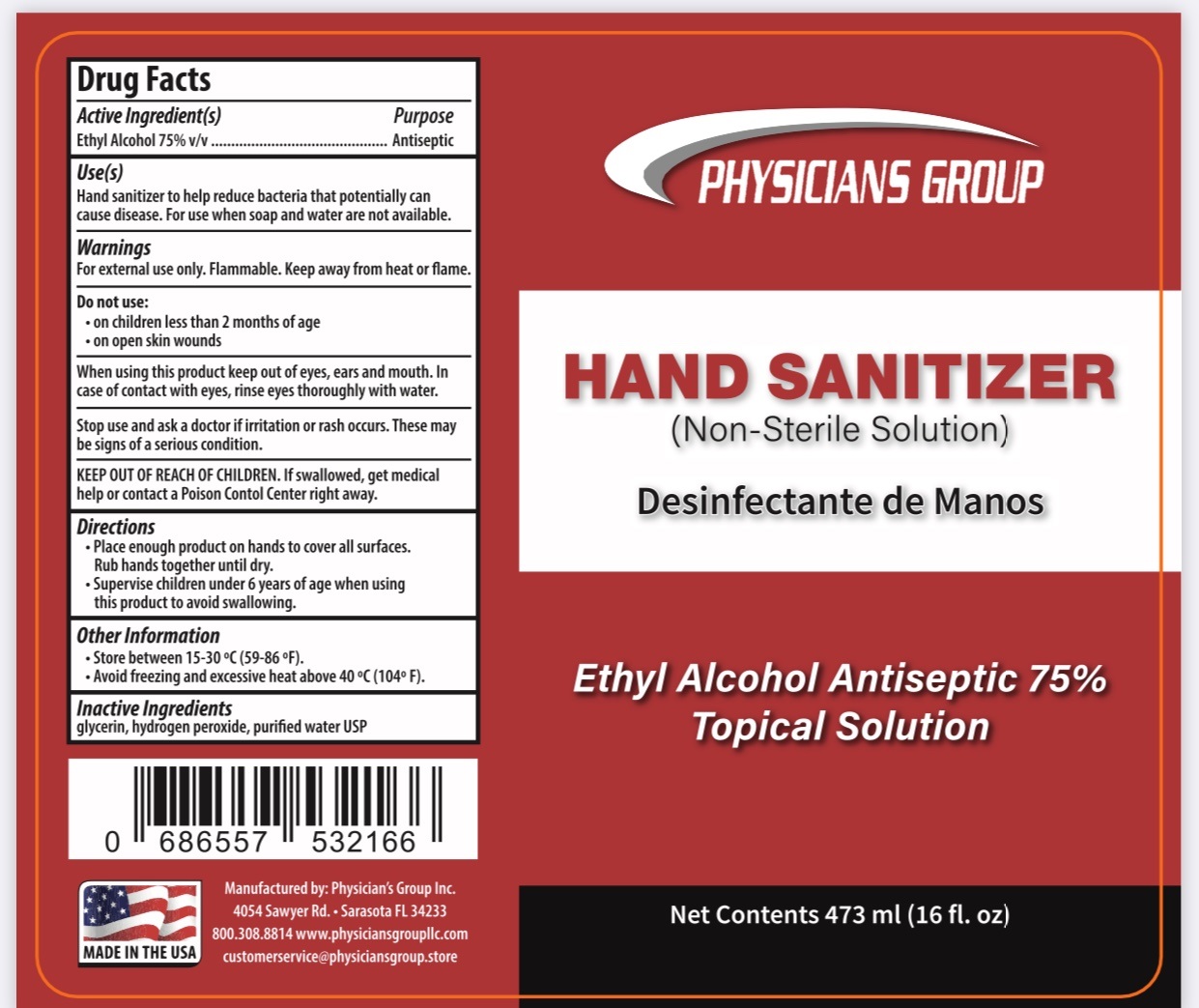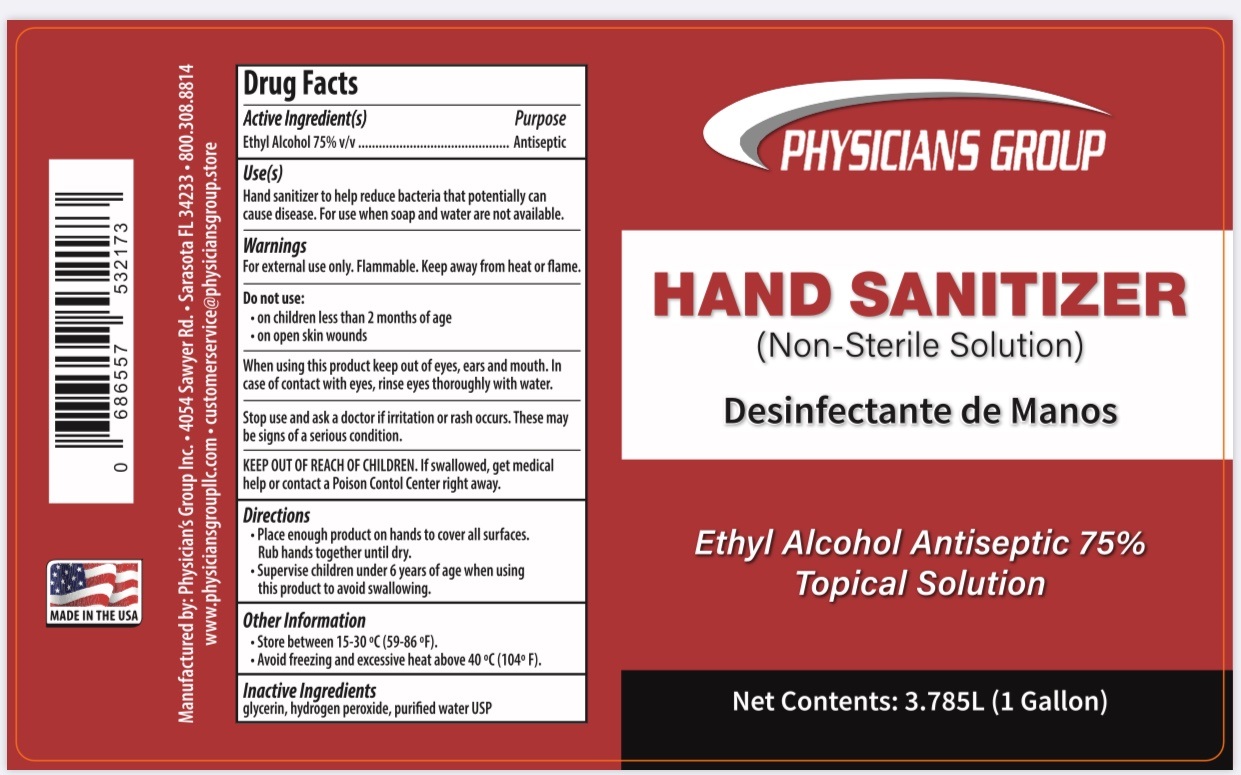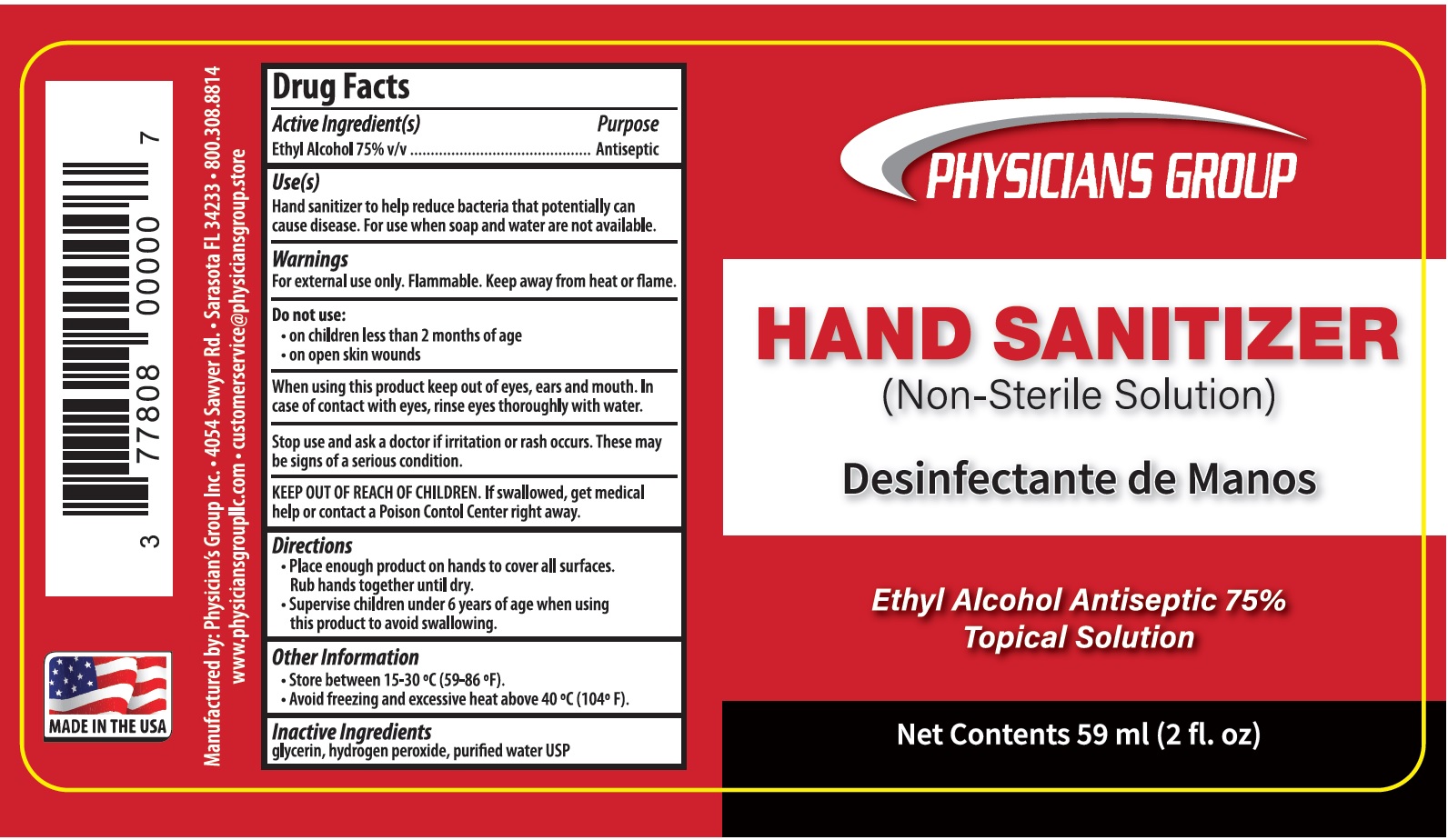 DRUG LABEL: Physicians Group Hand Sanitizer
NDC: 77808-001 | Form: LIQUID
Manufacturer: Physicians Group, L.L.C.
Category: otc | Type: HUMAN OTC DRUG LABEL
Date: 20231227

ACTIVE INGREDIENTS: ALCOHOL 0.75 mL/1 mL
INACTIVE INGREDIENTS: GLYCERIN; HYDROGEN PEROXIDE; WATER

Physicians Group Hand Sanitizer

Active Ingredient(s)

Ethyl Alcohol 75% v/v

Purpose

Antiseptic

Use(s)

Hand sanitizer to help reduce bacteria that potentially can cause disease. For use when soap and water are not availble.

Warnings

For external use only. Flammable. Keep away from heat or flame.

Do not use:

- on children less than 2 months of age
- on open skin wounds

When using this product

Keep out of eyes, ears and mouth. In case of contact with eyes rinse eyes thoroughly with water.

Stop use and ask a doctor

if irritation or rash occurs. These may be signs of a serious condition.

KEEP OUT OF REACH OF CHILDREN.

If swallowed, get medical help or contact a Poison Contol Center right away.

Directions

- Place enough product on hands to cover all surface. Rub hands together until dry.
- Supervise children under 6 years of age when using this product to avoid swallowing.

Other Information

- Store between 15-30°C(59-86°F)
- Avoid freezing and excessive heat above 40°C(104°F)

Inactive Ingredients

glycerin, hydrogen peroxide, purified water USP